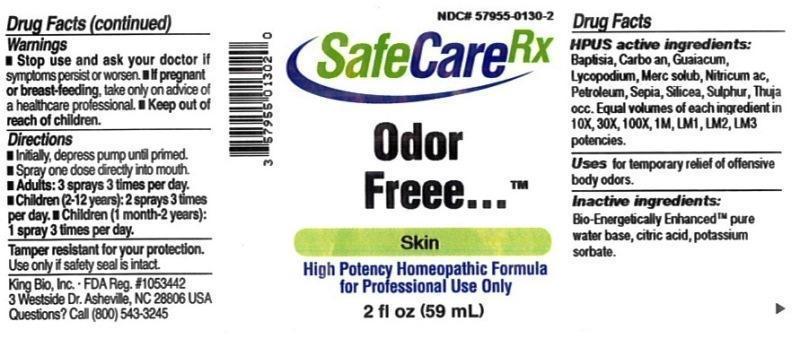 DRUG LABEL: Odor Freee
NDC: 57955-0130 | Form: LIQUID
Manufacturer: King Bio Inc.
Category: homeopathic | Type: HUMAN OTC DRUG LABEL
Date: 20150327

ACTIVE INGREDIENTS: BAPTISIA TINCTORIA ROOT 10 [hp_X]/59 mL; CARBO ANIMALIS 10 [hp_X]/59 mL; GUAIACUM OFFICINALE RESIN 10 [hp_X]/59 mL; LYCOPODIUM CLAVATUM SPORE 10 [hp_X]/59 mL; MERCURIUS SOLUBILIS 10 [hp_X]/59 mL; NITRIC ACID 10 [hp_X]/59 mL; KEROSENE 10 [hp_X]/59 mL; SEPIA OFFICINALIS JUICE 10 [hp_X]/59 mL; SILICON DIOXIDE 10 [hp_X]/59 mL; SULFUR 10 [hp_X]/59 mL; THUJA OCCIDENTALIS LEAFY TWIG 10 [hp_X]/59 mL
INACTIVE INGREDIENTS: WATER; ANHYDROUS CITRIC ACID; POTASSIUM SORBATE

Odor Freee™

ACTIVE INGREDIENT

Drug Facts__________________________________________________________________________________________________________

HPUS active ingredients: Baptisia tinctoria, Carbo animalis, Guaiacum, Lycopodium clavatum, Mercurius solubilis, Nitricum acidum, Petroleum, Sepia, Silicea, Sulphur, Thuja occidentalis. Equal volumes of each ingredient in 10X, 30X, 100X, 1M, LM1, LM2, LM3 potencies.

INDICATIONS AND USAGE

Uses for temporary relief of offensive body odors.

Inactive Ingredients:

Bio-Energetically Enhanced™ pure water, citric acid and potassium sorbate.

Warnings

- Stop use and ask your doctor if symptoms persist or worsen.
- If pregnant or breast-feeding, take only on advice of a healthcare professional.

- Keep out of reach of children.

Directions

- Initially, depress pump until primed.
- Spray one dose directly into mouth.
- Adults: 3 sprays 3 times per day.
- Children (2-12 years): 2 sprays 3 times per day.
- Children (1 month-2 years): 1 spray 3 times per day.

OTHER SAFETY INFORMATION

Tamper resistant for your protection. Use only if safety seal is intact.

PURPOSE

Uses for temporary relief of:

- offensive body odors